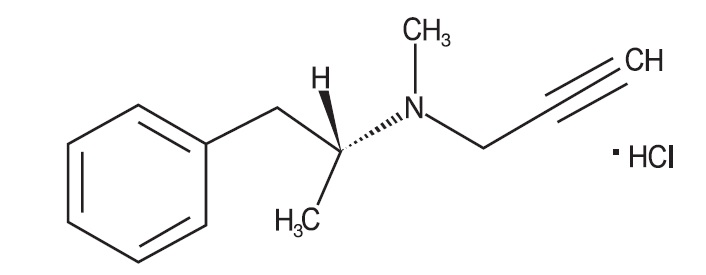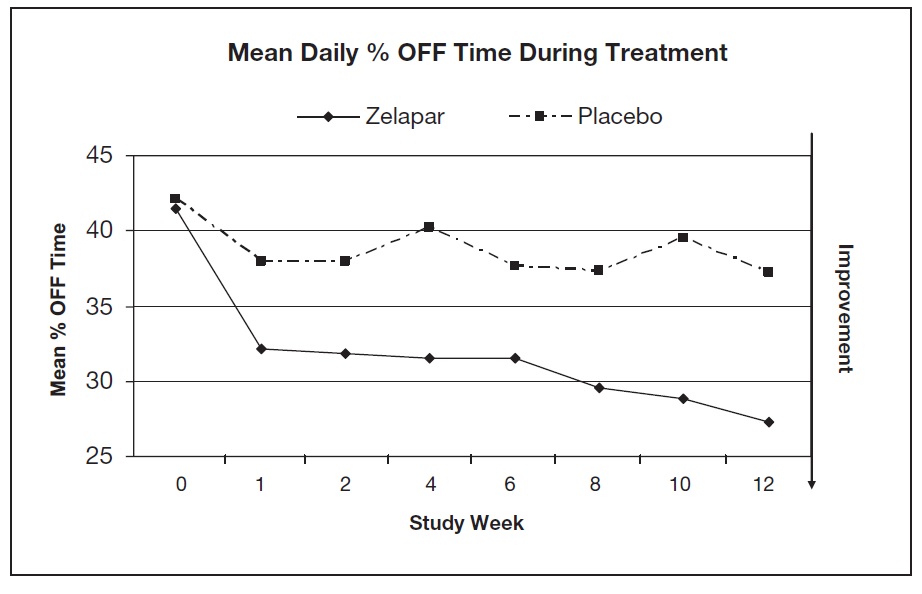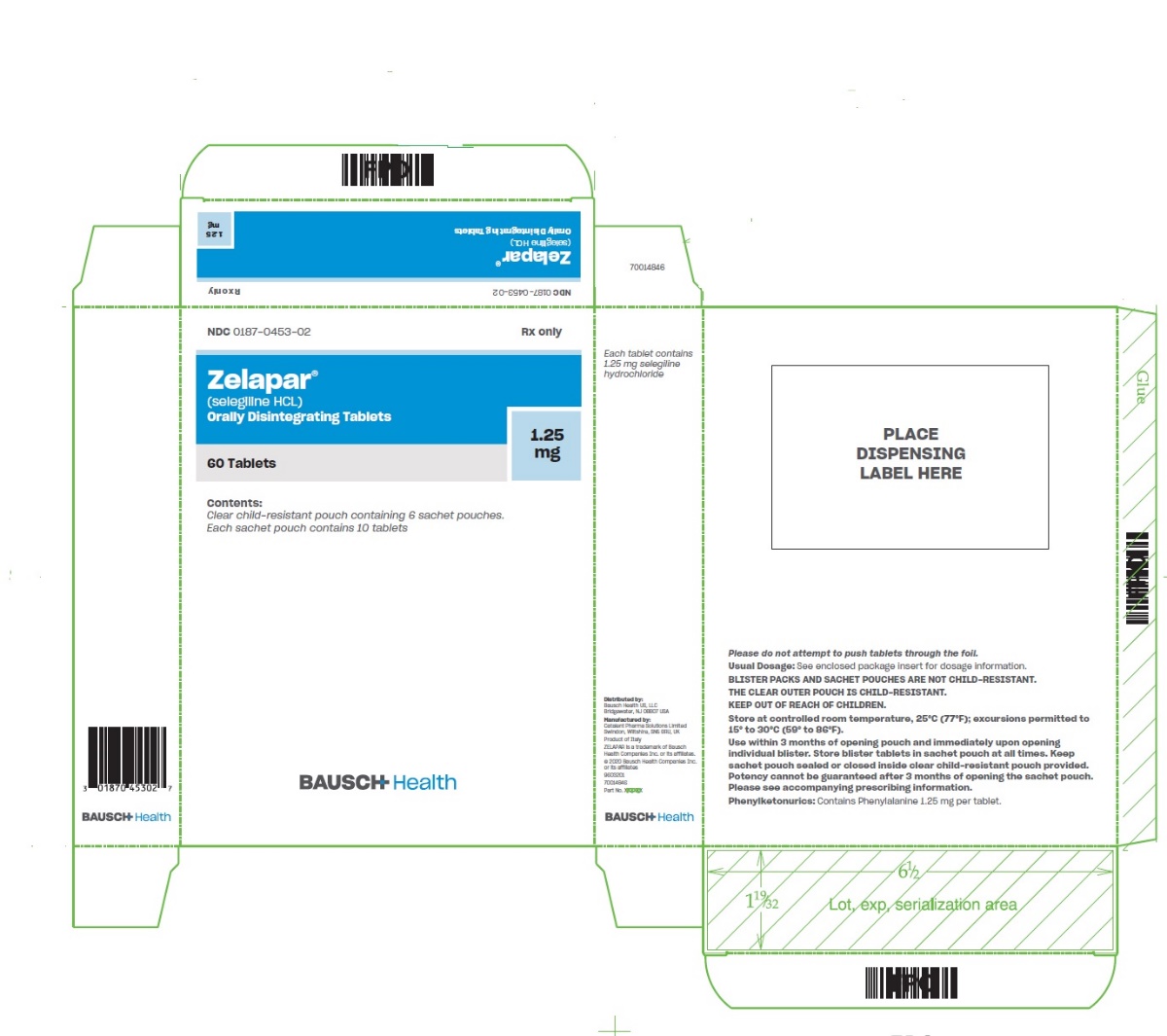 DRUG LABEL: ZELAPAR
NDC: 0187-0453 | Form: TABLET, ORALLY DISINTEGRATING
Manufacturer: Bausch Health US, LLC
Category: prescription | Type: HUMAN PRESCRIPTION DRUG LABEL
Date: 20210601

ACTIVE INGREDIENTS: SELEGILINE HYDROCHLORIDE 1.25 mg/1 1
INACTIVE INGREDIENTS: MANNITOL; GLYCERIN; ASPARTAME; CITRIC ACID MONOHYDRATE; FERRIC OXIDE YELLOW; GELATIN, UNSPECIFIED

HIGHLIGHTS OF PRESCRIBING INFORMATION

These highlights do not include all the information needed to use ZELAPAR safely and effectively. See full prescribing information for ZELAPAR.
ZELAPAR® (selegiline hydrochloride) orally disintegrating tablets
Initial U.S. Approval: 2006

RECENT MAJOR CHANGES

Contraindications (4) 6/2021

Warnings and Precautions,
  Melanoma-removal (5.9) 6/2021
  Risk for Patients with Phenylketonuria (5.10) 6/2021

1 INDICATIONS AND USAGE

ZELAPAR, a monoamine oxidase type B (MAO-B) inhibitor, is indicated as an adjunct in the management of patients with Parkinson’s disease being treated with levodopa/carbidopa who exhibit deterioration in the quality of their response to this therapy (1)

2 DOSAGE AND ADMINISTRATION

- Initiate treatment with 1.25 mg given once a day for at least 6 weeks; after 6 weeks, the dose may be escalated to 2.5 mg once a day (2.1)
- Place tablet on top of the tongue where the tablet will disintegrate in seconds; avoid food and liquid intake 5 minutes before and after each dose (2.1)
- In patients with mild or moderate hepatic impairment, the dose should be reduced to 1.25 mg; ZELAPAR is not recommended in patients with severe (Child-Pugh score >9) hepatic impairment (2.2)

3 DOSAGE FORMS AND STRENGTHS

Orally Disintegrating Tablets: 1.25 mg (3)

4 CONTRAINDICATIONS

ZELAPAR is contraindicated in patients using the following drugs: opioid drugs (e.g., meperidine, tramadol, methadone), MAO inhibitors including selective MAO-B inhibitors, dextromethorphan, St. John’s wort, and cyclobenzaprine (4)

5 WARNINGS AND PRECAUTIONS

- May cause hypertension above 2.5 mg/day (5.1)
- May cause serotonin syndrome when used with antidepressants (5.2)
- May cause falling asleep during activities of daily living (5.3)
- May cause hypotension/orthostatic hypotension (5.4)
- May cause or exacerbate dyskinesia (5.5)
- May cause hallucinations and psychotic-like behavior (5.6)
- May cause problems with impulse control and compulsive behaviors (5.7)
- Abrupt discontinuation may cause hyperpyrexia and confusion (5.8)
- May cause irritation of the buccal mucosa (5.9)
- Increased risk for patients with phenylketonuria (5.10)

6 ADVERSE REACTIONS

The most common adverse reactions (incidence at least 3% greater than on placebo) are constipation, skin disorders, vomiting, dizziness, dyskinesia, insomnia, dyspnea, myalgia, and rash (6.1)

To report SUSPECTED ADVERSE REACTIONS, contact Bausch Health US, LLC at 1-800-321-4576 or FDA at 1-800-FDA-1088 or www.fda.gov/medwatch.

8 USE IN SPECIFIC POPULATIONS

- Pregnancy: Based on animal data, may cause fetal harm (8.1)
- Renal Impairment: ZELAPAR is not recommended in patients with severe renal impairment (CLcr <30 mL/min) (2.3, 8.7)

FULL PRESCRIBING INFORMATION

1 INDICATIONS AND USAGE

ZELAPAR is indicated as an adjunct in the management of patients with Parkinson’s disease being treated with levodopa/carbidopa who exhibit deterioration in the quality of their response to this therapy. There is no evidence from controlled studies that ZELAPAR has any beneficial effect in the absence of concurrent levodopa therapy [see Clinical Studies (14)].

2 DOSAGE AND ADMINISTRATION

2.1 General Dosage Recommendations

Initiate treatment with 1.25 mg given once a day for at least 6 weeks. After 6 weeks, the dose may be increased to 2.5 mg given once a day if a desired benefit has not been achieved and the patient is tolerating ZELAPAR. There is no evidence that doses greater than 2.5 mg a day provide additional benefit, and they should ordinarily be avoided because of the potential increased risk of adverse events.

Take ZELAPAR in the morning before breakfast and without liquid. Patients should avoid ingesting food or liquids for 5 minutes before and after taking ZELAPAR.

Patients should not attempt to push ZELAPAR through the foil backing. Patients should PEEL BACK the backing of one or two blisters (as prescribed) with dry hands, and GENTLY remove the tablet(s). Patients should IMMEDIATELY place the ZELAPAR tablet(s) on top of the tongue where it will disintegrate in seconds.

2.2 Patients with Hepatic Impairment

In patients with mild to moderate hepatic disease (Child-Pugh score 5 to 9), the daily dose of ZELAPAR should be reduced (from 2.5 to 1.25 mg daily), depending on the clinical response. ZELAPAR is not recommended in patients with severe hepatic impairment (Child-Pugh score greater than 9) [see Use in Specific Populations (8.6) and Clinical Pharmacology (12.3)].

2.3 Patients with Renal Impairment

No dose adjustment of ZELAPAR is required in patients with mild to moderate renal impairment (creatinine clearance [CLcr] 30 to 89 mL/min). The maintenance dose of ZELAPAR (1.25 mg or 2.5 mg) is determined by the individual clinical response. ZELAPAR is not recommended in patients with severe renal impairment and patients with end-stage renal disease [ESRD] (creatinine clearance [CLcr] <30 mL/min) [see Use in Specific Populations (8.7) and Clinical Pharmacology (12.3)].

3 DOSAGE FORMS AND STRENGTHS

ZELAPAR Orally Disintegrating Tablets are pale yellow, imprinted with a stylized “V”, and contain 1.25 mg selegiline hydrochloride.

4 CONTRAINDICATIONS

ZELAPAR is contraindicated in patients with:

- Concomitant use of opioid drugs (e.g., meperidine, tramadol, or methadone). Serotonin syndrome, a potentially serious condition, which can result in death, has been reported with concomitant use of meperidine (e.g., Demerol and other trade names). At least 14 days should elapse between discontinuation of ZELAPAR and initiation of treatment with these medications [see Warnings and Precautions (5.2)].
- Concomitant use of other drugs in the monoamine oxidase inhibitor (MAOI) class or other drugs that are potent inhibitors of monoamine oxidase, including linezolid), because of an increased risk for hypertensive crisis [see Warnings and Precautions (5.1)]. At least 14 days should elapse between discontinuation of ZELAPAR and initiation of treatment with any MAO inhibitor.
- Concomitant use of St. John’s wort or cyclobenzaprine (a tricyclic muscle relaxant).
- Concomitant use of dextromethorphan, because of reported episodes of psychosis or bizarre behavior.

5 WARNINGS AND PRECAUTIONS

5.1 Hypertension

ZELAPAR should not be used at daily doses exceeding those recommended (2.5 mg/day) because of the risks associated with non-selective inhibition of MAO [see Drug Interactions (7.3) and Clinical Pharmacology (12.2)].

The selectivity of ZELAPAR for MAO-B may not be absolute even at the recommended daily dose of 2.5 mg daily. The selectivity of MAO-B inhibitors typically decreases, and it is ultimately lost as the dose is increased beyond recommended doses. Hypertensive reactions associated with ingestion of tyramine-containing foods have been reported even in patients taking the recommended daily dose of swallowed selegiline, a dose which is generally believed to be selective for MAO-B. Selectivity for MAO-B inhibition is gradually lost with increasing daily doses. An increase in tyramine sensitivity for blood pressure responses appears to begin at a dose of 5 mg ZELAPAR daily [see Drug Interactions (7.5)]. However, the precise dose at which ZELAPAR becomes a non-selective inhibitor of all MAO enzymes in individual patients is unknown.

Reports of hypertensive reactions have occurred in patients who ingested tyramine-containing consumables (i.e., food or drink) while receiving swallowed selegiline at the recommended dose (a dose believed to be relatively selective for MAO-B).

The safe use of ZELAPAR at doses above 2.5 mg daily without dietary tyramine restrictions has not been established.

A pharmacodynamic study showed increased tyramine sensitivity for increasing blood pressure and decreased selectivity for MAO-B with dosing above the recommended level (2.5 mg daily) [see Clinical Pharmacology (12.2)].

Uncontrolled hypertension has been reported when taking the recommended dose of swallowed selegiline and a sympathomimetic medication (ephedrine).

After starting ZELAPAR, monitor patients for new onset hypertension or exacerbation of hypertension that is not adequately controlled.

5.2 Serotonin Syndrome

Serotonin syndrome and hyperpyrexia have been reported with the combined treatment of an antidepressant (e.g., selective serotonin reuptake inhibitors-SSRIs, serotonin-norepinephrine reuptake inhibitors-SNRIs, tricyclic antidepressants, tetracyclic antidepressants, triazolopyridine antidepressants) and a non-selective MAOI (e.g., phenelzine, tranylcypromine) or selective MAO-B inhibitors, such as selegiline (ELDEPRYL), rasagiline (AZILECT), and olanzapine (Zydis) selegiline (ZELAPAR).

Serotonin syndrome is a potentially serious condition, which can result in death. Typical clinical signs and symptoms include behavioral and cognitive/mental status changes (e.g., confusion, hypomania, hallucinations, agitation, delirium, headache, and coma), autonomic effects (e.g., syncope, shivering, sweating, high fever/hyperthermia, hypertension, hypotension, tachycardia, nausea, diarrhea), and somatic effects (e.g., muscular rigidity, myoclonus, muscle twitching, hyperreflexia manifested by clonus, and tremor).

In the post-marketing period, fatal and non-fatal cases of serotonin syndrome have been reported in patients treated with antidepressants concomitantly with ZELAPAR [see Contraindications (4) and Drug Interactions (7.1, 7.2, 7.3)].

Clinical studies of ZELAPAR did not allow concomitant use of any selective serotonin re-uptake inhibitor (e.g., fluoxetine-Prozac, fluvoxamine-Luvox, paroxetine-Paxil, sertraline, venlafaxine-Effexor, or nefazodone-Serzone) or any non-selective serotonin reuptake inhibiting antidepressant drug (except when taken at a low dose and only at night for the purpose of effective sleep) with ZELAPAR.

Because the mechanisms responsible for these reactions are not fully understood, avoid the combination of ZELAPAR with any antidepressant. At least 14 days should elapse between discontinuation of ZELAPAR and initiation of treatment with a SSRI, SNRI, tricyclic, tetracyclic, or triazolopyridine antidepressant. In patients taking antidepressants with a long half-life (e.g., fluoxetine and its active metabolite), allow at least five weeks (perhaps longer, especially if fluoxetine has been prescribed chronically and/or at higher doses) to elapse between discontinuation of fluoxetine and initiation of ZELAPAR [see Drug Interactions (7.6)].

5.3 Falling Asleep During Activities of Daily Living and Somnolence

Patients with Parkinson’s disease treated with ZELAPAR or other drugs increasing dopaminergic tone have reported falling asleep while engaged in activities of daily living, including the operation of motor vehicles, which sometimes resulted in accidents. Although many of these patients reported somnolence, some did not perceive warning signs, such as excessive drowsiness, and believed that they were alert immediately prior to the event. Some of these events have been reported as late as one year after initiation of treatment.

It has been reported that falling asleep while engaged in activities of daily living always occurs in a setting of pre-existing somnolence, although patients may not give such a history. For this reason, prescribers should reassess patients for drowsiness or sleepiness especially since some of the events occur well after the start of treatment.

Somnolence may occur in patients receiving ZELAPAR. There was an increased risk for somnolence in geriatric patients (≥65 years) vs. non-geriatric patients treated with ZELAPAR. Prescribers should also be aware that patients may not acknowledge drowsiness or sleepiness until directly questioned about drowsiness or sleepiness during specific activities. Patients should be advised to exercise caution while driving, operating machines, or working at heights during treatment with ZELAPAR. Patients who have already experienced somnolence and/or an episode of sudden sleep onset should not participate in these activities during treatment with ZELAPAR.

Before initiating treatment with ZELAPAR, advise patients about the potential to develop drowsiness and specifically ask about factors that may increase this risk, such as concomitant sedating medications and the presence of sleep disorders. If a patient develops daytime sleepiness or episodes of falling asleep during activities that require active participation (e.g., conversations, eating, etc.), ZELAPAR should ordinarily be discontinued. If a decision is made to continue ZELAPAR, patients should be advised not to drive and to avoid other potentially dangerous activities. There is insufficient information to establish whether dose reduction will eliminate episodes of falling asleep while engaged in activities of daily living.

5.4 Hypotension/Orthostatic Hypotension

Assessments of orthostatic (supine and standing) blood pressures at different times throughout the 12 week study period in two controlled trials showed that the frequency of orthostatic hypotension (>20 mm Hg decrease in systolic blood pressure and/or >10 mm Hg decrease in diastolic blood pressure) was greater with ZELAPAR treatment than with placebo treatment. Patients taking ZELAPAR were most likely to experience a decline in systolic and diastolic blood pressure at 8 weeks (2 weeks after initiating 2.5 mg ZELAPAR). At that time, the incidence of systolic orthostatic hypotension was about 21% in ZELAPAR-treated patients and 9% in placebo-treated patients. The incidence of diastolic orthostatic hypotension was about 12% in ZELAPAR-treated patients and about 4% in placebo-treated patients. Thus, it appears that there may be an increased risk for orthostatic hypotension in the period after increasing the daily dose of ZELAPAR from 1.25 to 2.5 mg.

The incidence of orthostatic hypotension was higher in geriatric patients (≥65 years) than in non-geriatric patients. In the geriatric patients, orthostatic hypotension occurred in about 3% of ZELAPAR-treated patients compared to 0% of placebo-treated patients.

5.5 Dyskinesia

ZELAPAR may potentiate dopaminergic side effects of levodopa and may cause dyskinesia or exacerbate preexisting dyskinesia. In controlled trials, the incidence of dyskinesia was 6% in ZELAPAR-treated patients and 3% in placebo-treated patients. Decreasing the dose of levodopa may lessen dyskinesia. The incidence of dyskinesia causing study discontinuation was greater on ZELAPAR than on placebo.

5.6 Hallucinations/Psychotic-Like Behavior

In controlled trials, hallucination was reported by 4% of ZELAPAR-treated patients and 2% in placebo-treated patients. Hallucinations led to drug discontinuation and premature withdrawal from clinical trials in about 1% of ZELAPAR-treated patients, compared to no patient on placebo.

Postmarketing reports indicate that patients may experience new or worsening mental status and behavioral changes, which may be severe, including psychotic-like behavior during ZELAPAR treatment or after starting or increasing the dose of ZELAPAR. Other drugs prescribed to improve the symptoms of Parkinson’s disease can have similar effects on thinking and behavior. This abnormal thinking and behavior can consist of one or more of a variety of manifestations including paranoid ideation, delusions, hallucinations, confusion, psychotic-like behavior, disorientation, aggressive behavior, agitation, and delirium.

Patients with a major psychotic disorder should ordinarily not be treated with ZELAPAR because of the risk of exacerbating psychosis. In addition, certain medications used to treat psychosis may exacerbate the symptoms of Parkinson's disease and may decrease the effectiveness of ZELAPAR [see Drug Interactions (7.8)].

5.7 Impulse Control/Compulsive Behaviors

Case reports suggest that patients can experience intense urges to gamble, increased sexual urges, intense urges to spend money, binge eating, and/or other intense urges, and the inability to control these urges while taking one or more of the medications, including ZELAPAR, that increase central dopaminergic tone and that are generally used for the treatment of Parkinson’s disease. In some cases, although not all, these urges were reported to have stopped when the dose was reduced or the medication was discontinued. Because patients may not recognize these behaviors as abnormal, it is important for prescribers to specifically ask patients or their caregivers about the development of new or increased gambling urges, sexual urges, uncontrolled spending, binge eating, or other urges while being treated with ZELAPAR. Physicians should consider dose reduction or stopping the medication if a patient develops such urges while taking ZELAPAR.

5.8 Withdrawal Emergent Hyperpyrexia and Confusion

Although not reported with ZELAPAR in the clinical development program, a symptom complex resembling the neuroleptic malignant syndrome (characterized by elevated temperature, muscular rigidity, altered consciousness, and autonomic instability), with no other obvious etiology, has been reported in association with rapid dose reduction, withdrawal of, or changes in antiparkinsonian therapy.

5.9 Irritation of the Buccal Mucosa

In the controlled clinical trials, periodic examinations of the tongue and oral mucosa were performed. At the end of the study, the frequency of mild oropharyngeal abnormality (e.g., swallowing pain, mouth pain, discrete areas of focal reddening, multiple foci of reddening, edema, and/or ulceration) in patients without similar abnormality at baseline was 10% in ZELAPAR-treated patients compared to 3% in placebo-treated patients.

5.10 Risk for Patients with Phenylketonuria

Phenylalanine can be harmful to patients with phenylketonuria (PKU). ZELAPAR contains phenylalanine, a component of aspartame. Each ZELAPAR 1.25 mg tablet contains 1.25 mg phenylalanine. Patients taking the 2.5 mg dose of ZELAPAR will receive 2.5 mg phenylalanine. Before prescribing ZELAPAR to a patient with PKU, consider the combined daily amount of phenylalanine from all sources, including ZELAPAR.

6 ADVERSE REACTIONS

The following adverse reactions are discussed in more detail in the Warnings and Precautions section of labeling:

- Risk for Hypertension [see Warnings and Precautions (5.1)]
- Risk of Serotonin Syndrome [see Warnings and Precautions (5.2)]
- Falling Asleep During Activities of Daily Living and Somnolence [see Warnings and Precautions (5.3)]
- Hypotension/Orthostatic Hypotension [see Warnings and Precautions (5.4)]
- Dyskinesia [see Warnings and Precautions (5.5)]
- Hallucinations/Psychotic-Like Behavior [see Warnings and Precautions (5.6)]
- Impulse Control/Compulsive Behaviors [see Warnings and Precautions (5.7)]
- Withdrawal Emergent Hyperpyrexia and Confusion [see Warnings and Precautions (5.8)]
- Irritation of the Buccal Mucosa [see Warnings and Precautions (5.9)]
- Risk for Patients with Phenylketonuria [see Warnings and Precautions (5.10)]

6.1 Clinical Trials Experience

Because clinical trials are conducted under widely varying conditions, the incidence of adverse reactions (number of unique patients experiencing an adverse reaction per total number of patients treated) observed in the clinical trials of a drug cannot be directly compared to rates in the clinical trials of another drug and may not reflect the incidence of adverse reactions observed in clinical practice.

Because the controlled trials performed during premarketing development both used a titration design (1.25 mg per day for 6 weeks, followed by 2.5 mg per day for 6 weeks), with a resultant confounding of time and dose, it was impossible to adequately evaluate the effects of dose on the incidence of adverse reactions.

The most common adverse reactions (treatment difference incidence at least 3% greater than placebo incidence) reported in the double-blind, placebo-controlled trials during ZELAPAR treatment were constipation, skin disorders, vomiting, dizziness, dyskinesia, insomnia, dyspnea, myalgia, and rash (see Table 1).

Of the 194 patients treated with ZELAPAR in the double-blind, placebo-controlled trials, 5% discontinued due to adverse reactions compared to 1% of the 98 patients who received placebo. Most common adverse reactions causing discontinuation of treatment included dizziness, chest pain, accidental injury, and myasthenia.

Incidence in Controlled Clinical Trials

Table 1 lists the adverse reactions reported in the placebo-controlled trials after at least one dose of ZELAPAR (incidence 2% or greater).

Table 1: Adverse Reactions [Patients may have reported multiple adverse experiences during the study or at discontinuation; thus patients may be included in more than one category.] in Double-Blind, Placebo-Controlled Trials with an Incidence ≥2% of Patients Treated with ZELAPAR and More Frequent than the Placebo Group
Body System/ Adverse Event | ZELAPAR 1.25/2.5 mg N=194 % | Placebo N=98 %
Body as a Whole
Pain | 8 | 7
Back Pain | 5 | 3
Chest Pain | 2 | 0
Cardiovascular System
Hypertension | 3 | 2
Digestive System
Nausea | 11 | 9
Stomatitis | 5 | 4
Dyspepsia | 5 | 3
Constipation | 4 | 0
Vomiting | 3 | 0
Diarrhea | 2 | 1
Dysphagia | 2 | 1
Flatulence | 2 | 1
Tooth Disorder | 2 | 1
Hemic and Lymphatic System
Ecchymosis | 2 | 0
Metabolic and Nutritional Disorders
Hypokalemia | 2 | 0
Musculoskeletal System
Leg Cramps | 3 | 1
Myalgia | 3 | 0
Nervous System
Dizziness | 11 | 8
Headache | 7 | 6
Insomnia | 7 | 4
Dyskinesia | 6 | 3
Dry Mouth | 4 | 2
Hallucinations | 4 | 2
Somnolence | 3 | 2
Tremor | 3 | 1
Ataxia | 3 | 1
Depression | 2 | 1
Respiratory System
Pharyngitis | 4 | 2
Rhinitis | 7 | 6
Dyspnea | 3 | 0
Skin and Appendages
Rash | 4 | 1
Skin Disorders [Skin disorders represent any new skin abnormality that would not be characterized as rash or neoplastic lesion. These include events such as skin ulcer, fungal dermatitis, skin hypertrophy, contact dermatitis, herpes simplex, dry skin, sweating, urticaria, and pruritus.] | 6 | 2

Certain adverse reactions were reported at a higher frequency by patients ≥65 years of age compared to patients <65 years [see Use in Specific Populations (8.5)].

No consistent differences in the incidences of adverse reactions were observed between male and female patients.

There were insufficient data to assess the impact of race on the incidence of adverse reactions.

7 DRUG INTERACTIONS

7.1 Opioid Drugs

Because serious, sometimes fatal reactions have been precipitated with concomitant use of opioid drugs (e.g., meperidine and its derivatives, methadone, or tramadol) and MAOIs, including selective MAO-B inhibitors, concomitant use of these drugs with ZELAPAR is contraindicated [see Contraindications (4) and Warnings and Precautions (5.2)]. At least 14 days should elapse between discontinuation of ZELAPAR and initiation of treatment with these drugs.

7.2 Dextromethorphan

The combination of MAO inhibitors and dextromethorphan has been reported to cause brief episodes of psychosis or bizarre behavior. Therefore, in view of ZELAPAR’s MAO inhibitory activity, dextromethorphan should not be used concomitantly with ZELAPAR [see Contraindications (4)].

7.3 MAO Inhibitors

ZELAPAR is contraindicated for concomitant use with other drugs in the MAOI class or other drugs that are potent inhibitors of monoamine oxidase (including linezolid, an oxazolidinone antibacterial, which also has reversible nonselective MAO inhibition activity) because of the increased risk for hypertensive crisis [see Contraindications (4) and Warnings and Precautions (5.1)]. At least 14 days should elapse between discontinuation of ZELAPAR and initiation of treatment with other MAOIs.

7.4 Sympathomimetic Medications

Uncontrolled hypertension, including hypertensive crisis, has been reported when taking the recommended dose of swallowed selegiline and a sympathomimetic medication (ephedrine).

7.5 Tyramine/Selegiline Interaction

The enzyme, monoamine oxidase (MAO) (primarily type A), in the gastrointestinal tract and liver provides protection from ingested amines (e.g., tyramine) that, if absorbed, have the capacity to cause uncontrolled hypertension (tyramine reaction). If MAO is inhibited in the gastrointestinal tract and liver, ingestion of exogenous amines contained in some foods such as fermented cheese, herring, or over-the-counter cough/cold medicines may be absorbed systemically causing release of norepinephrine and a rise in systemic blood pressure with the potential for uncontrolled hypertension. Selective MAO-B inhibitors lose their selectivity for MAO-B when taken in doses higher than recommended. Non-selective MAO-A inhibitors or MAO-B inhibitors in higher than recommended doses may result in MAO-A inhibition in the gastrointestinal tract and liver.

Results of a tyramine challenge study indicate that ZELAPAR is relatively selective for MAO-B at the recommended dose. In most cases, there is no need for dietary tyramine restriction in patients prescribed ZELAPAR [see Clinical Pharmacology (12.2)] at the recommended dose. Because the selectivity for inhibiting MAO-B diminishes as the dose of ZELAPAR is increased above the recommended daily dose, patients should not take more than 2.5 mg of ZELAPAR daily.

Reports of hypertensive reactions have occurred in patients who ingested tyramine-containing consumables (i.e., food or drink) while receiving swallowed selegiline at the recommended dose (a dose believed to be relatively selective for MAO-B). Hypertensive crisis has also been reported with ZELAPAR use that was not above the recommended dosing.

Uncontrolled hypertension has been reported when taking the recommended dose of swallowed selegiline and a sympathomimetic medication (ephedrine).

7.6 Tricyclic Antidepressants and Selective Serotonin Reuptake Inhibitors

Severe toxicity has also been reported in patients receiving the combination of tricyclic antidepressants and swallowed selegiline, or selective serotonin reuptake inhibitors and swallowed selegiline [see Warnings and Precautions (5.2)].

7.7 Drugs that Induce CYP450

Adequate studies have not been done investigating the effect of CYP3A4 inducers on selegiline. Drugs that induce CYP3A4 (e.g., phenytoin, carbamazepine, nafcillin, phenobarbital, and rifampin) should be used with caution.

7.8 Dopaminergic Antagonists

It is possible that dopamine antagonists, such as antipsychotics or metoclopramide, could diminish the effectiveness of ZELAPAR.

8 USE IN SPECIFIC POPULATIONS

8.1 Pregnancy

Risk Summary

There are no adequate data on the developmental risk associated with the use of ZELAPAR in pregnant women. In animal studies, administration of selegiline during pregnancy was associated with developmental toxicity (decreased embryofetal and postnatal offspring growth and survival) at doses greater than those used clinically.

In the U.S. general population, the estimated background risk of major birth defects and of miscarriage in clinically recognized pregnancies is 2% to 4% and 15% to 20%, respectively. The background risk of major birth defects and miscarriage in the indicated population is unknown.

Data

Animal Data

In rats administered selegiline orally (5, 10, and 40 mg/kg/day) throughout the period of organogenesis, a decrease in fetal body weight was observed at the mid and high doses. The no-effect dose for embryofetal developmental toxicity in rats (5 mg/kg/day) is approximately 20 times the maximum recommended human dose (MRHD) of 2.5 mg/day on a mg/m^2 basis.

In rabbits administered selegiline orally (5, 30, and 60 mg/kg/day) throughout the period of organogenesis, embryolethality was observed at the highest dose tested and reduced fetal body weight was observed at the mid and high doses. The no-effect dose for embryofetal developmental toxicity in rabbits (5 mg/kg/day) is approximately 40 times the MRHD on a mg/m^2 basis.

In rats administered selegiline orally (0.3, 1, and 10 mg/kg/day) during gestation and lactation, decreases in offspring survival and body weights were observed at the highest dose tested. The no-effect dose for pre- and postnatal developmental toxicity (1 mg/kg/day) is approximately 4 times the MRHD on a mg/m^2 basis.

8.2 Lactation

Risk Summary

There are no data on the presence of selegiline or its metabolites in human milk, the effects on the breastfed infant, or the effects on milk production. Selegiline and metabolites were detected in rat milk at levels higher than those in maternal plasma.

Because of the potential for serious adverse reactions in breastfed infants from ZELAPAR, including the potential for hypertensive reactions, advise a woman that breastfeeding is not recommended during treatment with ZELAPAR and for 7 days after the final dose.

8.4 Pediatric Use

Safety and effectiveness in pediatric patients have not been established.

8.5 Geriatric Use

The overall incidence of adverse reactions was increased in geriatric patients (≥65 years) compared to non-geriatric patients (<65 years). Clinical studies did not include a sufficient number of geriatric subjects older than 75 years to determine whether they respond differently to ZELAPAR.

Analysis of adverse reaction incidence in each group was conducted to calculate and compare relative risk (ZELAPAR % / Placebo %) for each treatment. The relative risk was ≥2 fold higher for ZELAPAR treatment in the geriatric patients compared to the non-geriatric patients for hypertension, orthostatic/postural hypotension [see Warnings and Precautions (5.4)]. The incidence of orthostatic hypotension by measurement of blood pressure was also higher in geriatric patients than in non-geriatric patients. In the geriatric patients, the treatment difference for incidence of orthostatic hypotension determined by supine and standing blood measurements was 3%.

8.6 Hepatic Impairment

Patients with mild to moderate hepatic impairment (Child-Pugh score 5 to 9) may require a dose reduction of ZELAPAR (from 2.5 to 1.25 mg daily) depending on the clinical response. ZELAPAR is not recommended in patients with severe hepatic impairment (Child-Pugh score >9) [see Dosage and Administration (2.2) and Clinical Pharmacology (12.3)].

8.7 Renal Impairment

No dose adjustment of ZELAPAR is required in patients with mild to moderate renal impairment (creatinine clearance [CLcr] 30 to 89 mL/min). ZELAPAR is not recommended in patients with severe renal impairment and patients with end-stage renal disease [ESRD] (CLcr <30 mL/min) [see Dosage and Administration (2.3) and Clinical Pharmacology (12.3)].

10 OVERDOSAGE

10.1 Selegiline

Experience gained during development of the 5 mg swallowed dosage form reveals that some individuals exposed to doses of 600 mg of d,l-selegiline suffered severe hypotension and psychomotor agitation. Small increments in serum BUN and creatinine have been observed in patients who received ZELAPAR 10 mg daily (4 times the recommended dose).

Since the selective inhibition of MAO-B by ZELAPAR is achieved only at doses in the range recommended for the treatment of Parkinson’s disease (e.g., 2.5 mg/day), overdoses are likely to cause significant inhibition of both MAO-A and MAO-B. Consequently, the signs and symptoms of overdose may resemble those observed with marketed non-selective MAO inhibitors [e.g., tranylcypromine (PARNATE®), isocarboxazid (MARPLAN®), and phenelzine (NARDIL®)]. For this reason, in cases of overdose with selegiline, dietary tyramine restriction should be observed for several weeks to avoid the risk of a hypertensive reaction.

10.2 Overdose with Non-selective MAO Inhibitors

NOTE: The following description of presenting symptoms and clinical course is based upon overdose descriptions of non-selective MAO inhibitors and does not include information from patients who have overdosed on oral selegiline or ZELAPAR.

Characteristically, signs and symptoms of non-selective MAO inhibitor overdose may not appear immediately. Delays of up to 12 hours between ingestion of drug and the appearance of signs may occur. Importantly, the peak intensity of the syndrome may not be reached for upwards of a day following the overdose. Death has been reported following overdosage. Therefore, immediate hospitalization, with continuous patient observation and monitoring for a period of at least two days following the ingestion of such drugs in overdose, is strongly recommended.

The clinical picture of MAO inhibitor overdose varies considerably; its severity may be a function of the amount of drug consumed. The central nervous and cardiovascular systems are prominently involved.

Signs and symptoms of overdosage may include, alone or in combination, any of the following: drowsiness, dizziness, faintness, irritability, hyperactivity, agitation, severe headache, hallucinations, trismus, opisthotonos, convulsions, and coma; rapid and irregular pulse, hypertension, hypotension and vascular collapse; precordial pain, respiratory depression and failure, hyperpyrexia, diaphoresis, and cool, clammy skin.

10.3 Treatment or Management of Overdose

Treatment of overdose with non-selective MAO inhibitors is symptomatic and supportive. Induction of emesis or gastric lavage with instillation of charcoal slurry may be helpful in early poisoning, provided the airway has been protected against aspiration. Signs and symptoms of central nervous system stimulation, including convulsions, should be treated with diazepam, given slowly intravenously. Phenothiazine derivatives and central nervous system stimulants should be avoided. Hypotension and vascular collapse should be treated with intravenous fluids and, if necessary, blood pressure titration with an intravenous infusion of a dilute pressor agent. It should be noted that adrenergic agents may produce a markedly increased pressor response.

Support respiration, including management of the airway, use of supplemental oxygen, and mechanical ventilatory assistance, as required.

Body temperature should be monitored closely. Intensive management of hyperpyrexia may be required. Maintenance of fluid and electrolyte balance is essential.

11 DESCRIPTION

ZELAPAR Orally Disintegrating Tablets contain selegiline hydrochloride, a levorotatory acetylenic derivative of phenethylamine. Selegiline hydrochloride is described chemically as: (-)-(R)-N, α-dimethyl-N-2-propynylphenethylamine hydrochloride and its structural formula is:

Its empirical formula is C13H17N∙HCl, representing a molecular weight of 223.74. Selegiline hydrochloride is a white to almost white crystalline powder that is freely soluble in water and in methanol, slightly soluble in acetone.

ZELAPAR Orally Disintegrating Tablets are available for oral administration (not to be swallowed) in a strength of 1.25 mg. Each lyophilized orally disintegrating tablet contains the following inactive ingredients: aspartame, citric acid, gelatin, glycine, mannitol, opatint yellow, purified water, and grapefruit flavor.

12 CLINICAL PHARMACOLOGY

12.1 Mechanism of Action

Selegiline is an irreversible inhibitor of monoamine oxidase (MAO), which regulates the metabolic degradation of catecholamines and serotonin in the central nervous system and peripheral tissues. At recommended doses, selegiline is selective for MAO type B (MAO-B), the major form in the brain. Inhibition of MAO-B activity, by blocking the catabolism of dopamine, may result in increased dopamine levels; however, there is evidence that selegiline may act through other mechanisms to increase dopaminergic activity.

12.2 Pharmacodynamics

A pharmacodynamic study investigating daily ZELAPAR doses of 2.5 mg, 5 mg, and 10 mg for tyramine sensitivity showed that increased tyramine sensitivity resulting in increased blood pressure (because of MAO-A inhibition and decreased selectivity for MAO-B) occurred with dosing above the recommended level (2.5 mg daily). An increase in tyramine sensitivity for blood pressure responses appears to begin at a dose of 5 mg ZELAPAR daily [see Warnings and Precautions (5.1)].

12.3 Pharmacokinetics

Absorption

ZELAPAR disintegrates within seconds after placement on the tongue and is rapidly absorbed. Detectable levels of selegiline from ZELAPAR have been measured at 5 minutes after administration, the earliest time point examined.

Selegiline is more rapidly absorbed from the 1.25 or 2.5 mg dose of ZELAPAR (Tmax range: 10-15 minutes) than from the swallowed 5 mg selegiline tablet (Tmax range: 40-90 minutes). Mean (SD) maximum plasma concentrations of 3.34 (1.68) and 4.47 (2.56) ng/mL are reached after single dose of 1.25 and 2.5 mg ZELAPAR compared to 1.12 ng/mL (1.48) for the swallowed 5 mg selegiline tablets (given as 5 mg bid). On a dose-normalized basis, the relative bioavailability of selegiline from ZELAPAR is greater than from the swallowed formulation.

The pre-gastric absorption from ZELAPAR and the avoidance of first-pass metabolism results in higher concentrations of selegiline and lower concentrations of the metabolites compared to the 5 mg swallowed selegiline tablet.

Plasma Cmax and AUC of ZELAPAR were dose proportional at doses between 2.5 and 10 mg daily.

Food Effects

When ZELAPAR is taken with food, the Cmax and AUC of selegiline are about 60% of those seen when ZELAPAR is taken in the fasted state. Since ZELAPAR is placed on the tongue and absorbed through the oral mucosa, the intake of food and liquid should be avoided 5 minutes before and after ZELAPAR administration [see Dosage and Administration (2.1)].

Distribution
Up to 85% of plasma selegiline is reversibly bound to proteins.

Metabolism
Following a single dose, the median elimination half-life of selegiline was 1.3 hours at the 1.25 mg dose. Under steady-state conditions, the median elimination half-life increases to 10 hours. Upon repeat dosing, accumulation in the plasma concentration of selegiline is observed both with ZELAPAR and the swallowed 5 mg tablet. Steady state is achieved after 8 days.

Selegiline is metabolized in vivo to l-methamphetamine and N-desmethylselegiline and subsequently to l-amphetamine; which in turn are further metabolized to their hydroxymetabolites.

ZELAPAR also produces a smaller fraction of the administered dose recoverable as the metabolites than the conventional, swallowed formulation of selegiline.

In vitro metabolism studies indicate that CYP2B6 and CYP3A4 are involved in the metabolism of selegiline. CYP2A6 may play a minor role in the metabolism.

Elimination

Following metabolism in the liver, selegiline is excreted primarily in the urine as metabolites (mainly as l-methamphetamine) and as a small amount in the feces.

Specific Populations

Age: The effect of age on the pharmacokinetics of selegiline following ZELAPAR administration has not been adequately characterized.

Gender: There are no differences between male and female subjects in overall (AUC∞), time to maximum exposure (Tmax), and elimination half-life (t½) after administration of ZELAPAR. Female subjects have an approximate 25% decrease in Cmax compared to male subjects. However, since the overall exposure (AUC∞) is not different between the genders, this pharmacokinetic difference is not likely to be clinically relevant.

Race: No studies have been conducted to evaluate the effects of race on the pharmacokinetics of ZELAPAR.

Renal Impairment: Following once-daily dosing of ZELAPAR 2.5 mg to selegiline steady-state (10 days) in 6 subjects with mild renal impairment (CLcr >50 to 89 mL/min) and in 6 subjects with moderate renal impairment (CLcr >30 to 50 mL/min), AUC and Cmax of selegiline and desmethylselegiline were not substantially different from healthy subjects; however, methamphetamine and amphetamine exposures were increased by 34-67% in subjects with moderate renal impairment. Following once-daily dosing of ZELAPAR 1.25 mg to steady-state (10 days) in 6 end-stage renal disease patients, off dialysis, selegiline exposure was not substantially different from that in healthy subjects, however methamphetamine and amphetamine exposures were increased approximately 4-fold compared to healthy subjects [see Dosage and Administration (2.3) and Use in Specific Populations (8.7)].

Hepatic Impairment: Subjects with mild hepatic impairment (Child-Pugh score 5 to 6), received once-daily dosing of ZELAPAR 2.5 mg to selegiline until they attained steady-state (10 days). The AUC and Cmax of selegiline were 1.5-fold higher and the AUC and Cmax of the metabolite desmethylselegiline were 1.4-fold and 1.2-fold higher. In subjects with moderate hepatic impairment (Child-Pugh score 7 to 9), the AUC of selegiline and desmethylselegiline increased 1.5-fold and 1.8-fold, respectively, whereas the Cmax of selegiline and desmethylselegiline were comparable to healthy subjects. Patients with severe hepatic impairment (Child-Pugh score >9) had a 4-fold increased AUC of selegiline, 3-fold increased Cmax of selegiline, a 1.25-fold increased AUC of desmethylselegiline and 50% reduced Cmax of desmethylselegiline. Methamphetamine and amphetamine metabolite AUC values were not affected by liver dysfunction [see Dosage and Administration (2.2) and Use in Specific Populations (8.6)].

Drug Interactions

No studies have been conducted to evaluate drug interactions on the pharmacokinetics of ZELAPAR.

Effect of CYP3A inhibitor itraconazole: Itraconazole (200 mg once daily) did not affect the pharmacokinetics of selegiline (single 10 mg oral, swallowed dose).

Although adequate studies to investigate the effect of CYP3A4-inducers on selegiline have not been performed, drugs that induce CYP3A4 (e.g., phenytoin, carbamazepine, nafcillin, phenobarbital, and rifampin) should be used with caution.

Drug Interaction Studies

No drug interaction studies have been conducted to evaluate the effects of other drugs on the pharmacokinetics of ZELAPAR or the effect of selegiline on other drugs. In vitro studies have demonstrated that selegiline is not an inhibitor of CYP450 enzymes. Selegiline and two of its metabolites, methamphetamine and desmethylselegiline, have little or no potential to induce CYP1A2 and CYP3A4/5 under clinical conditions.

13 NONCLINICAL TOXICOLOGY

13.1 Carcinogenesis, Mutagenesis, Impairment of Fertility

Carcinogenesis

Carcinogenicity studies of orally administered selegiline are not available for ZELAPAR.

Carcinogenicity studies of selegiline have not been conducted using the buccal route.

Mutagenesis

Selegiline was negative in the in vitro bacterial reverse mutation (Ames) assay in and the in vivo micronucleus assay. In the in vitro chromosomal aberration assay in mammalian cells, selegiline was negative in the absence of metabolic activation but was clastogenic in the presence of metabolic activation.

Impairment of Fertility

When selegiline was administered orally to male (5, 10, and 40 mg/kg/day) and female (1, 5, and 25 mg/kg/day) rats prior to and during mating and continuing in females to gestation day 7, a decreased number of implantations was observed at the highest doses tested. In males, a reduction in sperm count and density was observed at the highest dose tested. The no-effect doses for reproductive impairment in rats (10 mg/kg/day in males and 5 mg/kg/day in females) are approximately 40 (males) and 20 (females) times the maximum recommended human dose of 2.5 mg/day on a mg/m^2 basis.

No fertility studies have been conducted with selegiline using the buccal route.

14 CLINICAL STUDIES

The effectiveness of ZELAPAR as an adjunct to levodopa/carbidopa in the treatment of Parkinson’s disease was established in a multicenter, randomized, placebo-controlled trial (n=140; 94 received ZELAPAR, 46 received placebo) of three months’ duration. Patients randomized to ZELAPAR received a daily dose of 1.25 mg for the first 6 weeks, and a daily dose of 2.5 mg for the last 6 weeks. All patients were treated with concomitant levodopa products and could additionally have been on concomitant dopamine agonists, anticholinergics, amantadine, or any combination of these during the trial. COMT (catechol-O-methyl-transferase) inhibitors were not allowed.

Patients with idiopathic Parkinson’s disease receiving levodopa were enrolled if they demonstrated an average of at least 3 hours of “OFF” time per day on weekly diaries collected during a 2-week screening period. The patients enrolled had a mean duration of Parkinson’s disease of 7 years, with a range from 0.3 years to 22 years.

At selected times during the 12-week study, patients were asked to record the amount of “OFF,” “ON,” “ON with dyskinesia,” or “sleep” time per day for two separate days during the week prior to each scheduled visit. The primary efficacy outcome was the reduction in average percentage daily “OFF” time during waking hours from baseline to the end of the trial (averaging results at Weeks 10 and 12). Both treatment groups had an average of 7 hours per day of “OFF” time at baseline. Table 2 shows the primary efficacy results. Patients treated with ZELAPAR had a 13% reduction from baseline in daily “OFF” time, compared with a 5% reduction for patients treated with placebo. ZELAPAR-treated patients had an average reduction from baseline of “OFF” time of 2.2 hours per day, compared with a reduction of 0.6 hours in placebo-treated patients.

Table 2: Mean Percentage Change from Baseline in Daily "Off" Hours at End of Treatment

(Average of Weeks 10 and 12) for Intent-to-Treat Population

Treatment | Change from Baseline
Placebo | - 5%
ZELAPAR | - 13%

Figure 1 shows the mean daily percent “OFF” time during treatment over the whole study period for patients treated with ZELAPAR vs. patients treated with placebo.

Figure 1: Mean Daily Percent "OFF" Time During Treatment Over the Whole Study Period for Patients Treated with ZELAPAR vs. Patients Treated with Placebo

Dosage reduction of levodopa was allowed during this study if dopaminergic side effects, including dyskinesia and hallucinations, emerged. In those patients who had levodopa dosage reduced, the dose was reduced on average by 24% in ZELAPAR-treated patients and by 21% in placebo-treated patients.

No difference in effectiveness based on age (patients >66 years old vs. <66 years) was detected. The treatment effect size in males was twice that in females, but, given the size of this single trial, this finding is of doubtful significance.

16 HOW SUPPLIED/STORAGE AND HANDLING

ZELAPAR Orally Disintegrating Tablets are available containing 1.25 mg selegiline hydrochloride in a Zydis® formulation. Each pale yellow tablet is imprinted with a stylized “V”. Ten tablets in a blister card are provided in a sachet pouch. The sachet pouch is stored inside a clear child-resistant outer pouch and is packaged in a carton. The blister card and sachet pouch are not child-resistant. The clear outer pouch is child-resistant.

ZELAPAR (selegiline hydrochloride) is available as:

NDC 0187-0453-02 1.25 mg per tablet carton of 6 sachet pouches (60 tablets)

Store at controlled room temperature, 25°C (77°F); excursions permitted to 15°C to 30°C (59°F to 86°F). Use within 3 months of opening pouch and immediately upon opening individual blister. Store blister tablets in sachet pouch at all times. Keep sachet pouch sealed or closed inside clear child-resistant pouch provided. Potency cannot be guaranteed after 3 months of opening the sachet pouch.

17 PATIENT COUNSELING INFORMATION

Hypertension and Non-selective Inhibition of MAO Above the Recommended Dose

Advise patients (or their caregivers) not to exceed the daily recommended dose of 2.5 mg. Explain the risk of using higher daily doses of ZELAPAR and provide a brief description of the hypertensive tyramine reaction provided. Rare hypertensive reactions with oral selegiline at recommended doses associated with dietary influences have been reported.

Inform patients (or their caregivers) about the potential for MAOI-induced hypertensive reactions and describe their signs and symptoms. Instruct patients to report, immediately, severe headache or other atypical or unusual symptoms not previously experienced or very high blood pressure.

The possibility exists that very tyramine-rich foods (e.g., aged cheese such as Stilton) could possibly cause an increase in blood pressure. Patients should be advised to avoid certain foods (e.g., aged cheese) containing a very large amount of tyramine while taking recommended doses of ZELAPAR because of the potential for large increases in blood pressure. If patients eat foods very rich in tyramine and do not feel well soon after eating, they should contact their healthcare provider [see Warnings and Precautions (5.1)].

Serotonin Syndrome

Inform patients if they are taking, or planning to take, any prescription or over-the-counter drugs, especially antidepressants and over-the-counter cold medications, because there is a potential for interaction with ZELAPAR. Because patients should not use meperidine or certain other analgesics with ZELAPAR, they should contact their healthcare provider before taking analgesics [see Warnings and Precautions (5.2)].

Falling Asleep During Activities of Daily Living and Somnolence

Advise patients about the potential for sedating effects associated with ZELAPAR, including somnolence and particularly to the possibility of falling asleep while engaged in activities of daily living. Because somnolence can be a frequent adverse reaction with potentially serious consequences, patients should neither drive a car nor engage in other potentially dangerous activities until they have gained sufficient experience with ZELAPAR to gauge whether or not it affects their mental and/or motor performance adversely. Advise patients that if they experience increased somnolence or new episodes of falling asleep during activities of daily living (e.g., watching television, passenger in a car, etc.) at any time during treatment, they should not drive or participate in potentially dangerous activities until they have contacted their physician. Advise patients not to drive, operate machinery, or work at heights during treatment if they have previously experienced somnolence and/or have fallen asleep without warning prior to use of ZELAPAR [see Warnings and Precautions (5.3)].

Hypotension/Orthostatic Hypotension

Advise patients that they may develop symptomatic (or asymptomatic) hypotension while taking ZELAPAR, especially if they are elderly. Hypotension may occur more frequently during initial therapy. Accordingly, caution patients against rising rapidly after sitting or lying down, especially if they have been doing so for prolonged periods and especially at the initiation of treatment with ZELAPAR [see Warnings and Precautions (5.4)].

Dyskinesia

Inform patients that ZELAPAR may cause and/or exacerbate pre-existing dyskinesias [see Warnings and Precautions (5.5)].

Hallucinations/Psychotic-Like Behavior

Inform patients that hallucinations and other psychotic-like behavior can occur while taking ZELAPAR and that the elderly are at a higher risk than younger patients with Parkinson's disease. Tell patients to report hallucinations or psychotic-like behavior to their healthcare provider promptly should they develop [see Warnings and Precautions (5.6)].

Impulse Control/Compulsive Behaviors

Advise patients that they may experience impulse control and/or compulsive behaviors while taking one or more of the medications generally used for the treatment of Parkinson’s disease, including ZELAPAR. Although it is not proven that the medications caused these events, these urges were reported to have stopped in some cases when the dose was reduced or the medication was stopped. Prescribers should ask patients about the development of new or increased gambling urges, sexual urges or other urges while being treated with ZELAPAR. Patients should inform their physician if they experience new or increased gambling urges, increased sexual urges or other intense urges while taking ZELAPAR. Physicians should consider dose reduction or stopping the medication if a patient develops such urges while taking ZELAPAR [see Warnings and Precautions (5.7)].

Withdrawal Emergent Hyperpyrexia and Confusion

Advise patients to contact their healthcare provider if they wish to discontinue ZELAPAR or decrease the dose of ZELAPAR [see Warnings and Precautions (5.8)].

Irritation of the Buccal Mucosa

Inform patients that ZELAPAR may cause irritation of the buccal mucosa including swallowing pain, mouth pain, discrete areas of focal reddening, edema, and/or ulceration [see Warnings and Precautions (5.9)].

Risk for Phenylketonuric Patients

Advise patients that ZELAPAR contains aspartame which could cause problems in patients with phenylketonuria [see Warnings and Precautions (5.10)].

Instructions for Use

Instruct patients not to remove the blister from the sachet pouch until just prior to dosing. The blister pack should then be peeled open with dry hands and the orally disintegrating tablet placed on the tongue, where the tablet will disintegrate. Patients should also avoid drinking liquids or eating food 5 minutes before and after taking ZELAPAR. Use ZELAPAR within 3 months of opening sachet pouch and immediately upon opening individual blister. Store blister tablets in sachet pouch at all times. Keep sachet pouch inside clear child-resistant pouch provided. Potency cannot be guaranteed after 3 months of opening the pouch.

How should I store ZELAPAR?

- Store ZELAPAR at controlled room temperature 25°C (77°F).
- Store blister tablets in sachet pouch at all times.
- Keep sachet pouch sealed or closed inside of clear child-resistant pouch provided.
- Potency cannot be guaranteed after 3 months of opening the sachet pouch.
- Keep ZELAPAR and all medicines out of the reach of children.

BLISTER PACKS AND SACHET POUCHES ARE NOT CHILD-RESISTANT. THE CLEAR OUTER POUCH IS CHILD-RESISTANT.

Distributed by:
Bausch Health US, LLC
Bridgewater, NJ 08807 USA
Manufactured by:
Catalent Pharma Solutions Limited
Swindon, Wiltshire, SN5 8RU, UK
ZELAPAR is a trademark of Bausch Health Companies Inc. or its affiliates.
Zydis is a registered trademark of Catalent Pharma Solutions or its affiliates.
All other product/brand names are trademarks of the respective owners.
© 2021 Bausch Health Companies Inc. or its affiliates
9603102

PACKAGE/LABEL PRINCIPAL DISPLAY PANEL

NDC 0187-0453-02
Rx only
Zelapar®
(selegiline HCL)
Orally Disintegrating Tablets
60 Tablets
1.25 mg
Contents:
Clear child-resistant pouch containing 6 sachetpouches.
Each sachet pouch contains 10 tablets
BAUSCH HEALTH